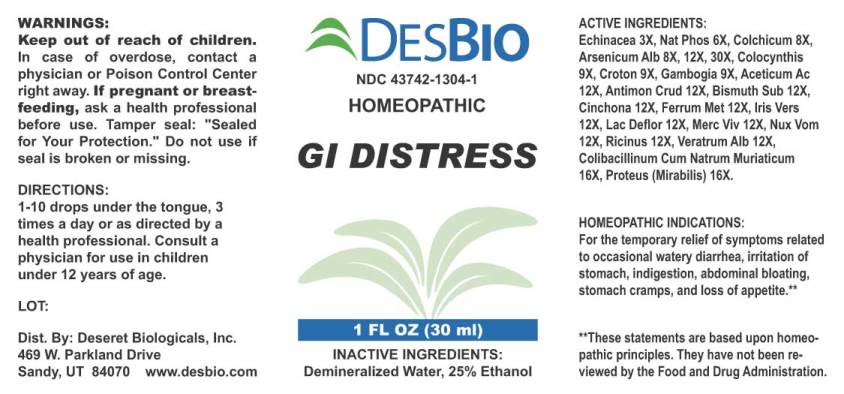 DRUG LABEL: GI Distress
NDC: 43742-1304 | Form: LIQUID
Manufacturer: Deseret Biologicals, Inc.
Category: homeopathic | Type: HUMAN OTC DRUG LABEL
Date: 20240508

ACTIVE INGREDIENTS: ECHINACEA ANGUSTIFOLIA WHOLE 3 [hp_X]/1 mL; SODIUM PHOSPHATE, DIBASIC, HEPTAHYDRATE 6 [hp_X]/1 mL; COLCHICUM AUTUMNALE BULB 8 [hp_X]/1 mL; ARSENIC TRIOXIDE 8 [hp_X]/1 mL; CITRULLUS COLOCYNTHIS FRUIT PULP 9 [hp_X]/1 mL; CROTON TIGLIUM SEED 9 [hp_X]/1 mL; GAMBOGE 9 [hp_X]/1 mL; ACETIC ACID 12 [hp_X]/1 mL; ANTIMONY TRISULFIDE 12 [hp_X]/1 mL; BISMUTH SUBNITRATE 12 [hp_X]/1 mL; CINCHONA OFFICINALIS BARK 12 [hp_X]/1 mL; IRON 12 [hp_X]/1 mL; IRIS VERSICOLOR ROOT 12 [hp_X]/1 mL; SKIM MILK 12 [hp_X]/1 mL; MERCURY 12 [hp_X]/1 mL; STRYCHNOS NUX-VOMICA SEED 12 [hp_X]/1 mL; RICINUS COMMUNIS SEED 12 [hp_X]/1 mL; VERATRUM ALBUM ROOT 12 [hp_X]/1 mL; ESCHERICHIA COLI 16 [hp_X]/1 mL; PROTEUS MIRABILIS 16 [hp_X]/1 mL
INACTIVE INGREDIENTS: WATER; ALCOHOL

Drug Facts:

ACTIVE INGREDIENTS:

Echinacea (Angustifolia) 3X, Natrum Phosphoricum 6X, Colchicum Autumnale 8X, Arsenicum Album 8X, 12X 30X, Colocynthis 9X, Croton Tiglium 9X, Gambogia 9X, Aceticum Acidum 12X, Antimonium Crudum 12X, Bismuthum Subnitricum 12X, Cinchona Officinalis 12X, Ferrum Metallicum 12X, Iris Versicolor 12X, Lac Defloratum 12X, Mercurius Vivus 12X, Nux Vomica 12X, Ricinus Communis 12X, Veratrum Album 12X, Colibacillinum Cum Natrum Muriaticum 16X, Proteus (Mirabilis) 16X.

HOMEOPATHIC INDICATIONS:

For the temporary relief of symptoms related to occasional watery diarrhea, irritation of stomach, indigestion, abdominal bloating, stomach cramps, and loss of appetite.**

**These statements are based upon traditional homeopathic principles. They have not been reviewed by the Food and Drug Administration.

WARNINGS:

Keep out of reach of children. In case of overdose, contact physician or Poison Control Center right away.

If pregnant or breast-feeding, ask a health professional before use.

Tamper seal: "Sealed for Your Protection." Do not use if seal is broken or missing.

Keep out of reach of children. In case of overdose, contact physician or Poison Control Center right away.

DIRECTIONS:

1-10 drops under the tongue, 3 times a day or as directed by a health professional. Consult a physician for use in children under 12 years of age.

HOMEOPATHIC INDICATIONS:

For the temporary relief of symptoms related to occasional watery diarrhea, irritation of stomach, indigestion, abdominal bloating, stomach cramps, and loss of appetite.**

**These statements are based upon traditional homeopathic principles. They have not been reviewed by the Food and Drug Administration.

INACTIVE INGREDIENTS:

Demineralized Water, 25% Ethanol.

QUESTIONS:

Dist. By: Deseret Biologicals, Inc.
469 W. Parkland Drive
Sandy, UT 84070 www.desbio.com

PACKAGE LABEL DISPLAY:

DESBIO

NDC 43742-1304-1

HOMEOPATHIC

GI DISTRESS

1 FL OZ (30 ml)